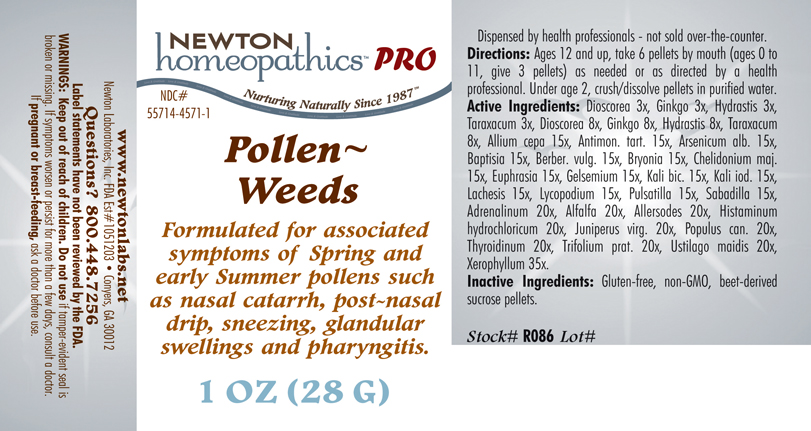 DRUG LABEL: Pollen - Weeds 
NDC: 55714-4571 | Form: PELLET
Manufacturer: Newton Laboratories, Inc.
Category: homeopathic | Type: HUMAN PRESCRIPTION DRUG LABEL
Date: 20110601

ACTIVE INGREDIENTS: Xerophyllum Asphodeloides 35 [hp_X]/1 g; Epinephrine 20 [hp_X]/1 g; Alfalfa 20 [hp_X]/1 g; Aletris Farinosa Root 20 [hp_X]/1 g; Artemisia Vulgaris Root 20 [hp_X]/1 g; Bellis Perennis 20 [hp_X]/1 g; Dysphania Ambrosioides 20 [hp_X]/1 g; Lycopus Virginicus 20 [hp_X]/1 g; Phytolacca Americana Root 20 [hp_X]/1 g; Populus Tremuloides Leaf 20 [hp_X]/1 g; Populus Tremuloides Bark 20 [hp_X]/1 g; Ptelea Trifoliata Bark 20 [hp_X]/1 g; Sambucus Nigra Flowering Top 20 [hp_X]/1 g; Trillium Erectum Root 20 [hp_X]/1 g; Elymus Repens Root 20 [hp_X]/1 g; Urtica Urens 20 [hp_X]/1 g; Wyethia Helenioides Root 20 [hp_X]/1 g; Yucca Filamentosa 20 [hp_X]/1 g; Avena Sativa Pollen 20 [hp_X]/1 g; Cynosurus Cristatus Pollen 20 [hp_X]/1 g; Echinochloa Crus-galli Pollen 20 [hp_X]/1 g; Poa Pratensis Pollen 20 [hp_X]/1 g; Agrostis Gigantea Pollen 20 [hp_X]/1 g; Bromus Secalinus Pollen 20 [hp_X]/1 g; Alopecurus Pratensis Pollen 20 [hp_X]/1 g; Phleum Pratense Pollen 20 [hp_X]/1 g; Festuca Pratensis Pollen 20 [hp_X]/1 g; Holcus Lanatus Pollen 20 [hp_X]/1 g; Lolium Perenne Pollen 20 [hp_X]/1 g; Fagus Sylvatica Pollen 20 [hp_X]/1 g; Betula Pendula Pollen 20 [hp_X]/1 g; Quercus Alba Pollen 20 [hp_X]/1 g; Fraxinus Excelsior Pollen 20 [hp_X]/1 g; Corylus Americana Pollen 20 [hp_X]/1 g; Populus Nigra Pollen 20 [hp_X]/1 g; Platanus Orientalis Pollen 20 [hp_X]/1 g; Ulmus Glabra Pollen 20 [hp_X]/1 g; Salix Alba Pollen 20 [hp_X]/1 g; Narcissus Pseudonarcissus 20 [hp_X]/1 g; Rosa Canina Flower 20 [hp_X]/1 g; Lilium Candidum Flower 20 [hp_X]/1 g; Primula Vulgaris 20 [hp_X]/1 g; Dianthus Caryophyllus Flower 20 [hp_X]/1 g; Ulex Europaeus Flower 20 [hp_X]/1 g; Cytisus Scoparius Pollen 20 [hp_X]/1 g; Calluna Vulgaris Pollen 20 [hp_X]/1 g; Crataegus Monogyna Pollen 20 [hp_X]/1 g; Histamine Dihydrochloride 20 [hp_X]/1 g; Juniperus Virginiana Twig 20 [hp_X]/1 g; Populus Balsamifera Leaf Bud 20 [hp_X]/1 g; Thyroid, Unspecified 20 [hp_X]/1 g; Trifolium Pratense Flower 20 [hp_X]/1 g; Ustilago Maydis 20 [hp_X]/1 g; Onion 15 [hp_X]/1 g; Antimony Potassium Tartrate 15 [hp_X]/1 g; Arsenic Trioxide 15 [hp_X]/1 g; Baptisia Tinctoria Root 15 [hp_X]/1 g; Berberis Vulgaris Root Bark 15 [hp_X]/1 g; Bryonia Alba Root 15 [hp_X]/1 g; Chelidonium Majus 15 [hp_X]/1 g; Euphrasia Stricta 15 [hp_X]/1 g; Gelsemium Sempervirens Root 15 [hp_X]/1 g; Potassium Dichromate 15 [hp_X]/1 g; Potassium Iodide 15 [hp_X]/1 g; Lachesis Muta Venom 15 [hp_X]/1 g; Lycopodium Clavatum Spore 15 [hp_X]/1 g; Pulsatilla Vulgaris 15 [hp_X]/1 g; Schoenocaulon Officinale Seed 15 [hp_X]/1 g; Dioscorea Villosa Tuber 8 [hp_X]/1 g; Ginkgo 8 [hp_X]/1 g; Goldenseal 8 [hp_X]/1 g; Taraxacum Officinale 8 [hp_X]/1 g; Anthoxanthum Odoratum Pollen 20 [hp_X]/1 g
INACTIVE INGREDIENTS: Sucrose

Pollen - Weeds

INDICATIONS & USAGE SECTION

Formulated for associated symptoms of Spring and early Summer pollens such as nasal catarrh, post-nasal drip, sneezing, glandular swellings and pharyngitis.

DOSAGE & ADMINISTRATION SECTION

Directions: Ages 12 and up, take 6 pellets by mouth (ages 0 to 11, give 3 pellets) as needed or as directed by a health professional. Under age 2, crush/dissolve pellets in purified water.

OTC - ACTIVE INGREDIENT SECTION

Xerophyllum asphodeloides 35, Adrenalinum 20x, Alfalfa 20x, Allersodes 20x, Histaminum hydrochloricum 20x, Juniperus virg. 20x, Populus can. 20x, Thyroidinum 20x, Trifolium prat. 20x, Ustilago maidis 20x, Allium cepa 15x, Antimon. tart. 15x, Arsenicum alb. 15x, Baptisia 15x, Berber. vulg. 15x, Bryonia 15x, Chelidonium majus 15x, Euphrasia 15x, Gelsemium 15x, Kali bic. 15x, Kali iod. 15x, Lachesis 15x, Lycopodium 15x, Pulsatilla 15x, Sabadilla 15x, Dioscorea 8x, Ginkgo 8x, Hydrastis 8x, Taraxacum 8x, Dioscorea 3x, Ginkgo 3x, Hydrastis 3x, Taraxacum 3x.

OTC - PURPOSE SECTION

Formulated for associated symptoms of Spring and early Summer pollens such as nasal catarrh, post-nasal drip, sneezing, glandular swellings and pharyngitis.

INACTIVE INGREDIENT SECTION

Inactive Ingredients: Gluten-free, non-GMO, beet-derived sucrose pellets.

QUESTIONS SECTION

www.newtonlabs.net Newton Laboratories, Inc. FDA Est # 1051203 - Conyers, GA 30012
Questions? 1.800.448.7256

WARNINGS SECTION

Warnings: Keep out of reach of children. Do no use if tamper-evident seal is broken or missing. If symptoms worsen or persist for more than a few days, consult a doctor. If pregnant or breast-feeding, ask a doctor before use.

OTC - PREGNANCY OR BREAST FEEDING SECTION

If pregnant or breast-feeding, ask a doctor before use.

OTC - KEEP OUT OF REACH OF CHILDREN SECTION

Keep out of reach of children.